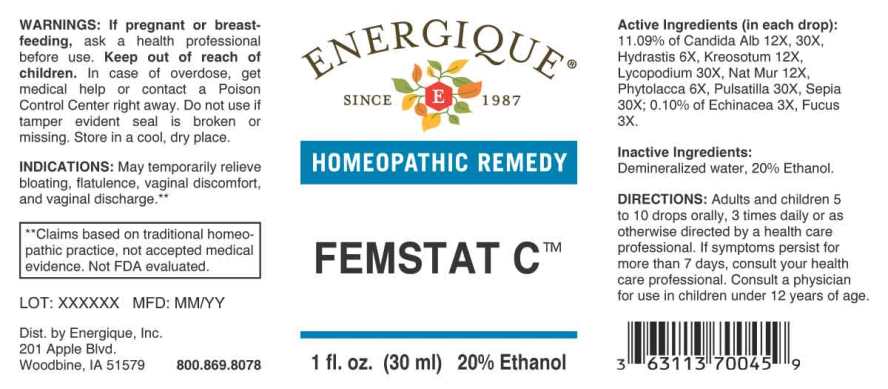 DRUG LABEL: Femstat C
NDC: 44911-0607 | Form: LIQUID
Manufacturer: Energique, Inc.
Category: homeopathic | Type: HUMAN OTC DRUG LABEL
Date: 20241024

ACTIVE INGREDIENTS: ECHINACEA ANGUSTIFOLIA WHOLE 3 [hp_X]/1 mL; FUCUS VESICULOSUS 3 [hp_X]/1 mL; GOLDENSEAL 6 [hp_X]/1 mL; PHYTOLACCA AMERICANA ROOT 6 [hp_X]/1 mL; WOOD CREOSOTE 12 [hp_X]/1 mL; SODIUM CHLORIDE 12 [hp_X]/1 mL; CANDIDA ALBICANS 12 [hp_X]/1 mL; LYCOPODIUM CLAVATUM SPORE 30 [hp_X]/1 mL; PULSATILLA PRATENSIS WHOLE 30 [hp_X]/1 mL; SEPIA OFFICINALIS JUICE 30 [hp_X]/1 mL
INACTIVE INGREDIENTS: WATER; ALCOHOL

DRUG FACTS:

ACTIVE INGREDIENTS:

(in each drop): 11.09% of Candida Albicans 12X, 30X, Hydrastis Canadensis 6X, Kreosotum 12X, Lycopodium Clavatum 30X, Natrum Muriaticum 12X, Phytolacca Decandra 6X, Pulsatilla (Pratensis) 30X, Sepia 30X; 0.10% of Echinacea (Angustifolia) 3X, Fucus Vesiculosus 3X.

INDICATIONS:

For temporary relief of bloating of the stomach, flatulence and rhinitis.**

**These statements are based upon traditional homeopathic practice. They have not been reviewed by the Food and Drug Administration.

WARNINGS:

If pregnant or breast-feeding, ask a health professional before use.

Keep out of reach of children. In case of overdose, get medical help or contact a Poison Control Center right away.

Do not use if tamper evident seal is broken or missing. Store in a cool, dry place.

Keep out of reach of children. In case of overdose, get medical help or contact a Poison Control Center right away.

DIRECTIONS:

Adults and children 5 to 10 drops orally, 3 times daily or as otherwise directed by a health care professional. If symptoms persist, consult your health care professional.
Consult a physician for use in children under 12 years of age.

INDICATIONS:

For temporary relief of bloating of the stomach, flatulence and rhinitis.**

**These statements are based upon traditional homeopathic practice. They have not been reviewed by the Food and Drug Administration.

INACTIVE INGREDIENTS:

Demineralized Water, 20% Ethanol

QUESTIONS:

Dist. by Energique, Inc.
201 Apple Blvd
Woodbine, IA 51579 800-869-8078

PACKAGE LABEL DISPLAY:

ENERGIQUE

SINCE 1987

HOMEOPATHIC REMEDY

FEMSTAT C

1 fl. oz. (30 ml)